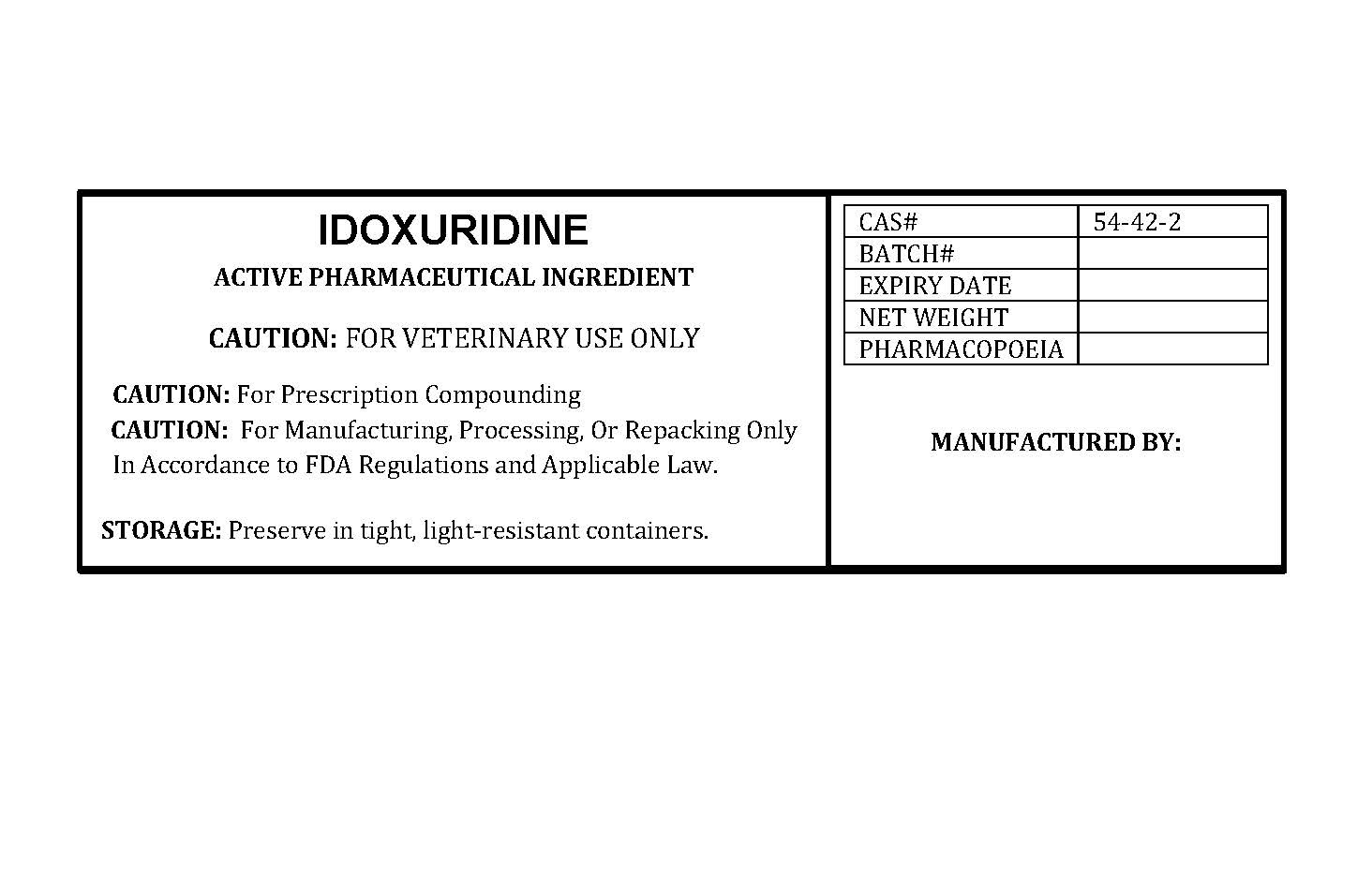 DRUG LABEL: IDOXURIDINE
NDC: 86184-161 | Form: POWDER
Manufacturer: MAEDA INC
Category: other | Type: BULK INGREDIENT - ANIMAL DRUG
Date: 20251028

ACTIVE INGREDIENTS: IDOXURIDINE 1 g/1 g

IDOXURIDINE

PACKAGE LABEL

idoxuridinelabelfile.jpg